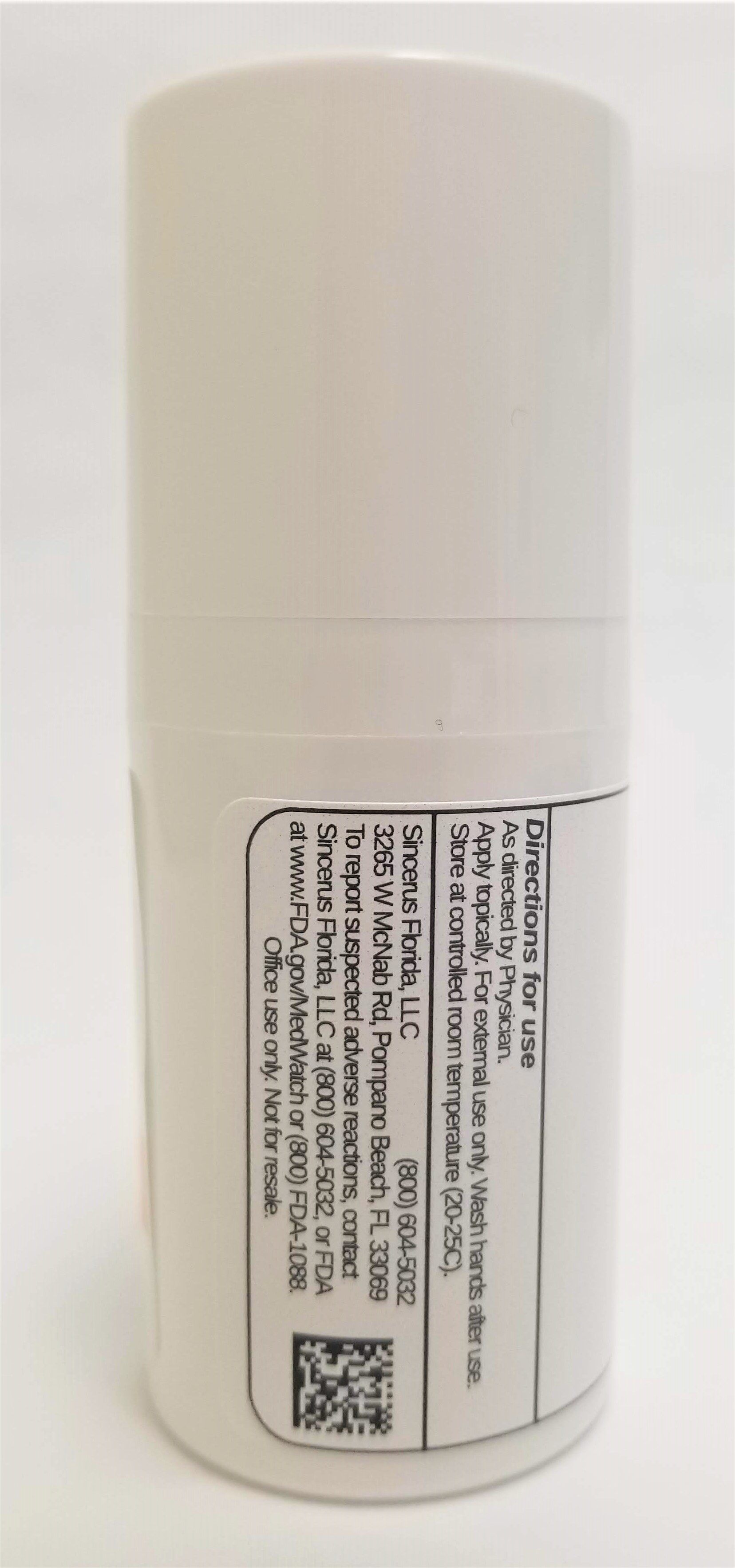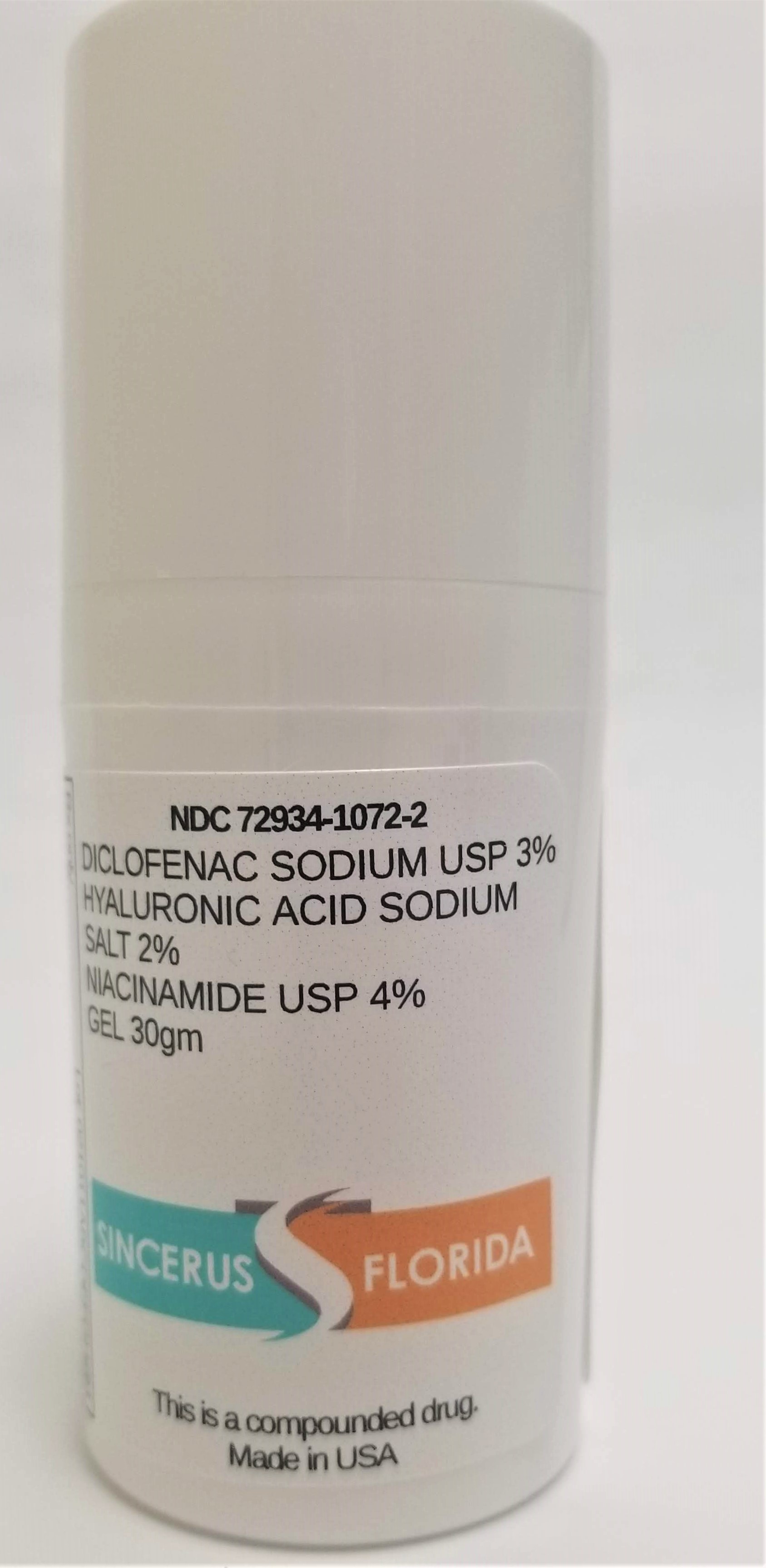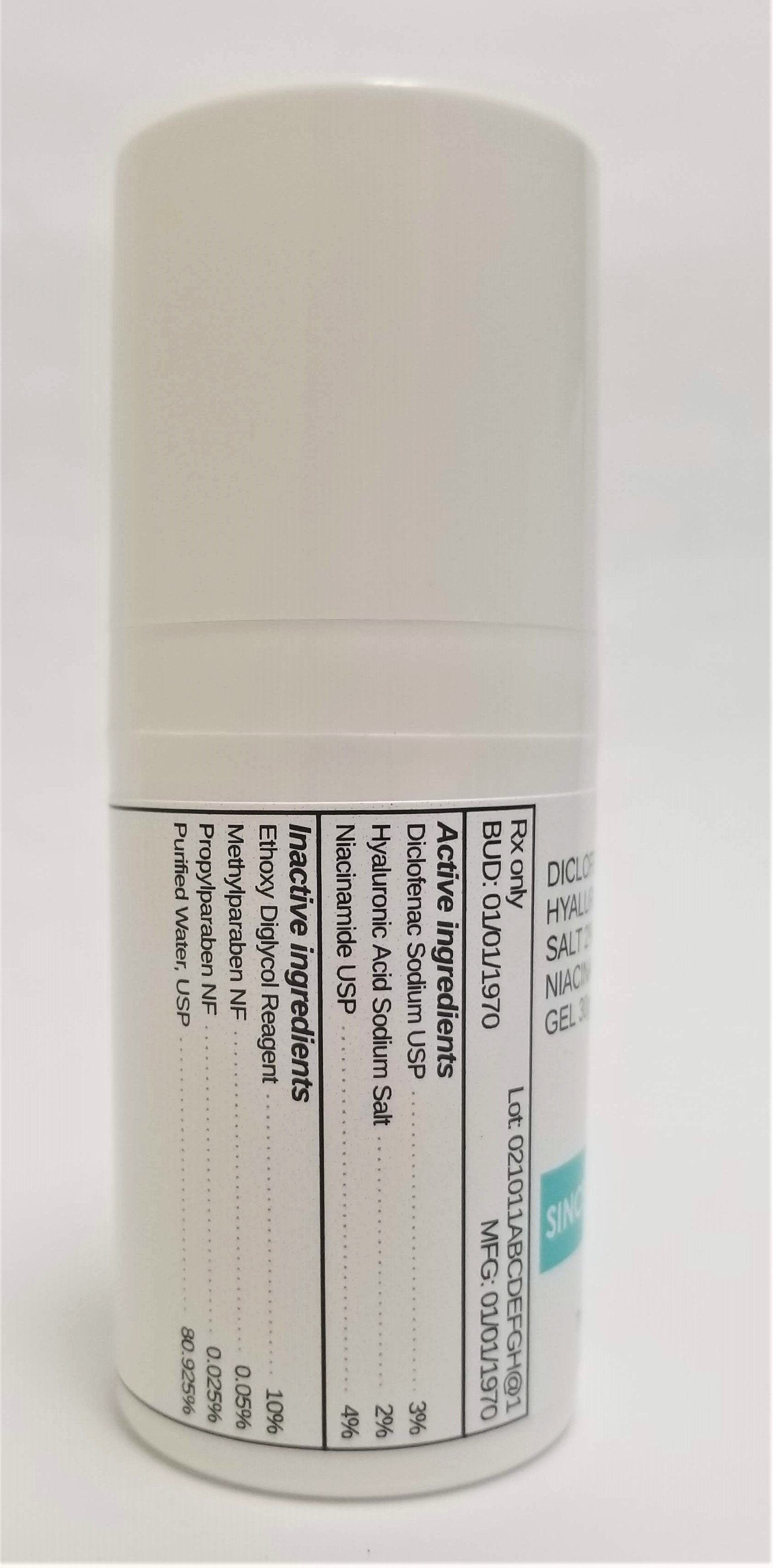 DRUG LABEL: DICLOFENAC SODIUM 3% / HYALURONIC ACID SODIUM SALT 2% / NIACINAMIDE 4%
NDC: 72934-1072 | Form: GEL
Manufacturer: Sincerus Florida, LLC
Category: prescription | Type: HUMAN PRESCRIPTION DRUG LABEL
Date: 20190506

ACTIVE INGREDIENTS: DICLOFENAC SODIUM 3 g/100 g

DICLOFENAC SODIUM 3% / HYALURONIC ACID SODIUM SALT 2% / NIACINAMIDE 4%